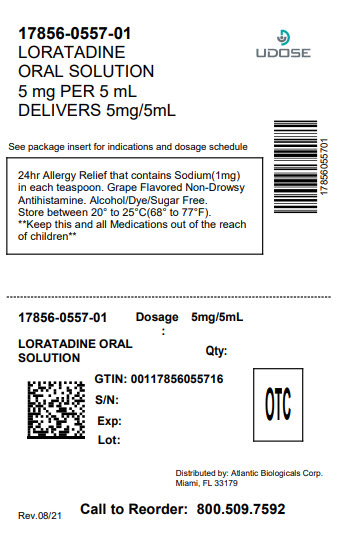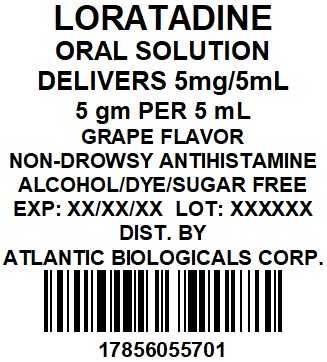 DRUG LABEL: Loratadine
NDC: 17856-0557 | Form: SOLUTION
Manufacturer: ATLANTIC BIOLOGICALS CORP.
Category: otc | Type: HUMAN OTC DRUG LABEL
Date: 20260226

ACTIVE INGREDIENTS: LORATADINE 5 mg/5 mL
INACTIVE INGREDIENTS: ANHYDROUS CITRIC ACID; BUTYLATED HYDROXYANISOLE; GLYCERIN; PROPYLENE GLYCOL; SODIUM BENZOATE; SUCRALOSE; WATER

Children's Loratadine Oral Solution

Active Ingredient: Loratadine 5 mg (in each 5 mL(teaspoonful)(TSP))

Purpose: Antihistamine

Uses

temporarily relieves these symptoms due to hay fever or other upper respiratory allergies:

- runny nose
- itchy, watery eyes
- sneezing
- itching of the nose or throat

Warnings

Do not use if you haveever had allergic reaction to this product or any of it's ingredients

Ask a doctor before use if you haveliver or kidney disease. Your doctor should determine if you need a different dose.

WHEN USING

When using this productdo not take more than directed. Taking more than directed may cause drowsiness.

Stop use and ask a doctor ifan allergic reaction to this product occurs. Seek medical help right away.

PREGNANCY OR BREAST FEEDING

If pregnant or breast-feeding, ask a health professional before use.

Keep out of reach of children. In case of overdose, get medical help or contact a Poison Control Center right away.

Directions

adults and children 6 years and over | 2 teaspoonfuls (TSP) daily; do not take more than 2 teaspoonfuls (TSP) in 24 hours
children 2 to under 6 years of age | 1 teaspoonful (TSP) daily; do not take more than 1 teaspoonful (TSP) in 24 hours
children under 2 years of age | ask a doctor
consumers with liver or kidney disease | ask a doctor

Other information

- Each teaspoonful contains: sodium 1 mg
- Safety Sealed. Do not use if imprinted seal around cap is broken or missing
- Store between 20° to 25°C (68° to 77°F)

Inactive ingredients

Butylated hydroxylanisole, citric acid, glycerin, grape flavor, propylene glycol, purified water, sodium benzoate, sucralose.

Questions

DISTRIBUTED BY:

ATLANTIC BIOLOGICALS CORP.

MIAMI, FL 33179

Active Ingredient: Loratadine 5 mg (in each 5 mL(teaspoonful(tsp)))

Purpose: Antihistamine

Uses

- relieves itching due to hives (urticaria). This product will not prevent hives or an allergic skin reaction from occurring.

Warnings

Severe Allergy Warning: Get emergency help immediatelyif you have hives along with any of the following symptoms:

- trouble swallowing
- dizziness or loss of consciousness
- swelling of tongue
- swelling in or around mouth
- trouble speaking
- drooling
- wheezing or problems breathing

These symptoms may be signs of anaphylactic shock. This condition can be life threatening if not treated by a health professional immediately. Symptoms of anaphylactic shock may occur when hives first appear or up to a few hours later.

Not a Substitute for Epinephrine. If your doctor has prescribed an epinephrine injector for “anaphylaxis” or severe allergy symptoms that could occur with your hives, never use this product as a substitute for the epinephrine injector. If you have been prescribed an epinephrine injector, you should carry it with you at all times.

Do not use

- to preventhives from any known cause such as:

- foods
- insects stings
- medicines
- latex or rubber gloves

because this product will not stop hives from occurring. Avoiding the cause of your hives is the only way to prevent them. Hives can sometimes be serious. If you do not know the cause of your hives, see your doctor for a medical exam. Your doctor may be able to help you find a cause.

- if you have ever had an allergic reaction to this product (loratadine) or any of its ingredients

Ask a doctor before use if you have

- liver or kidney disease. Your doctor should determine if you need a different dose.
- hives that are an unusual color, look bruised or blistered
- hives that do not itch

WHEN USING

When using this productdo not take more than directed. Taking more than directed may cause drowsiness.

Stop use and ask a doctor if

- an allergic reaction to this product occurs. Get medical help right away
- symptoms don’t improve after 3 days of treatment
- the hives have lasted more than 6 weeks

PREGNANCY OR BREAST FEEDING

If pregnant or breast-feeding, ask a health professional before use.

Keep out of reach of children. In case of overdose, get medical help or contact a Poison Control Center right away.

Directions

adults and children 6 years and over | 2 teaspoonfuls (tsp) daily; do not take more than 2 teaspoonfuls (tsp) in 24 hours
children under 6 years of age | ask a doctor
consumers with liver or kidney disease | ask a doctor

Other information

- Safety sealed. Do not use if imprinted seal around cap is broken or missing
- Store between 20° to 25°C (68° to 77°F)

Inactive ingredients

Butylated hydroxyanisole, citric acid, glycerin, grape flavor, propylene glycol, purified water, sodium benzoate, sucralose.

Questions

DISTRIBUTED BY:

ATLANTIC BIOLOGICALS CORP.

MIAMI, FL 33179

Patient Leaflet

Once Daily / Non-Drowsy*
Loratadine Oral Solution
Hives Relief
5 mg per 5 mL
Antihistamine

What you should know about:
Non- Drowsy*
Loratadine Oral Solution – Hives Relief
Original Prescription Strength – 24 Hour Product

Relief of Itching Due to Hives
(Please read all of this information before taking Loratadine Oral Solution – Hives Relief Product. Save this leaflet for future reference.)

What is Loratadine Oral Solution - Hives Relief product?

Loratadine Oral Solution - Hives Relief product contain loratadine, a non-drowsy *antihistamine.

Loratadine Oral Solution – Hives Relief
Original prescription strength medicine to relieve itching due to hives.

What are hives and what do they look like?
Hives are itchy raised red or pink bumps, blotches or streaky areas of various sizes on the surface of the skin. They can come and go.
Do not use this product if your hives look bruised, have an unusual color, or look blistered. These may be signs of a more serious problem. If you have these signs, ask a Doctor before taking Loratadine Oral Solution -Hives Relief product.
What can cause hives? Many things, including food, drugs (medicines), insect stings, stress, exercise or temperature can cause hives. A doctor may be able to help you find the cause of your hives. When you know the cause, avoid it.
Do not use this product to prevent hives or allergic skin reactions known to be caused by food, insect stings, medicines, latex or rubber gloves, or any other causes. Many medicines can cause hives.
How long do hives last? Hives can last from a few hours to a few weeks, and often come and go. See a doctor if your hives have lasted more than 6 weeks.
Are hives very serious?
Hives are very common and they are usually not serious. But in rare cases, they can be the first sign of a life threatening allergic reactioncalled anaphylaxis. A sign that you have this serious reaction would be that you have hives along with any of the following symptoms:

- Dizziness or feeling faint
- Trouble swallowing
- Wheezing or problems breathing
- Trouble speaking
- Hives or swelling in or around the mouth
- Drooling

Hives AND any of these symptoms means call 911 or Get Immediate Medical Help
Can I use Loratadine Oral Solution -Hives Relief product instead of an epinephrine injection for my allergic reaction?
Never use Loratadine Oral Solution – Hives Relief product as a substitute for epinephrine. If your doctor has prescribed an epinephrine injector for your severe allergic reactions, your doctor is concerned that your hives might lead to a severe allergic reaction (anaphylaxis) or to asthma-like symptoms that could occur with your hives. Loratadine Oral Solution – Hives Relief product is not a substitute for epinephrine. If you have been prescribed an epinephrine injector, carry it with you at all times.
Who can take Loratadine Oral Solution – Hives Relief Product?
People who have hives (urticaria) and are 6 years of age or older can take Loratadine Oral Solution – Hives Relief product. (See label Directions for proper dose.)
Who should not take Loratadine Oral Solution – Hives Relief Product?

- People who have ever had an allergic reaction to these products or any of their ingredients.
- People who are taking any other products containing loratadine
- People with liver or kidney disease unless directed by a doctor
- Children under the age of 6 years.

What if I know the cause of my hives and I want to take Loratadine Oral Solution – Hives Relief Product to prevent the hives from occurring?
Loratadine Oral Solution – Hives Relief product should never be used to prevent hives or allergic skin reactions from any known cause. Such causes can include but are not limited to:

- Food
- Insect Stings
- Medicines
- Latex or rubber gloves.

If you have ever had an allergic reaction to any of these causes, you should see a doctor.
When should you contact a doctor?
Contact a doctor before taking Loratadine Oral Solution – Hives Relief product if you have:

- Hives that have an unusual color or that look bruised or blistered
- Hives that have lasted longer than 6 weeks

If you are pregnant or breast feeding, you should ask a doctor or health professional before use.
Contact a doctor while taking Loratadine Oral Solution – Hives Relief Productif you (or your child) have:

- A rash or itching that does not get better after taking Loratadine Oral Solution – Hives Relief product for 3 days
- Hives that keep coming back.

How long can Loratadine Oral Solution – Hives Relief product be taken to relieve the itching?
Loratadine Oral Solution – Hives Relief product can be taken during the entire time that you have itching due to hives (see Directions). Don’t forget, if the hives last longer than 6 weeks, contact your doctor.
How should Loratadine Oral Solution – Hives Relief product be taken?

- Adults and children 6 years and older should take 2 teaspoonfuls of Loratadine Oral Solution (10 mg) daily.
- Do not take more than one dose in 24 hour period.
- If you have liver or kidney disease, ask a doctor.

What else can I do to make the itching and rash feel better?
Wear loose clothing to help reduce irritation. Keeping the temperature cool can help with the itching.
Other important information:

- Allergy Alert: Do not use if you are allergic to loratadine, any of its ingredients, or other antihistamines.
- If you have been prescribed an epinephrine injector, you should carry it with you at all times.
- Keep out of reach of children.
- In case of an overdose, get medical help or contact a Poison Control Center right away.

* When taken as directed. See drug facts panel on carton.

PACKAGE LABEL

NDC 17856-0557-1